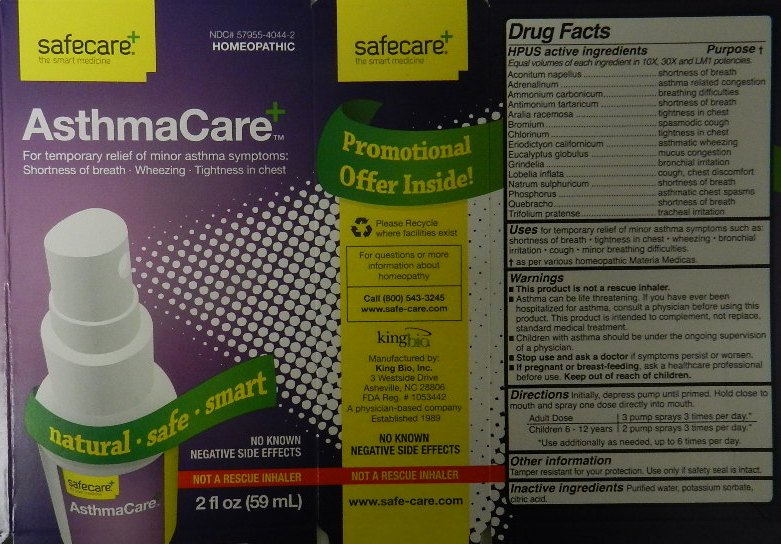 DRUG LABEL: AsthmaCare
NDC: 57955-4044 | Form: LIQUID
Manufacturer: King Bio Inc. 
Category: homeopathic | Type: HUMAN OTC DRUG LABEL
Date: 20120220

ACTIVE INGREDIENTS: ACONITUM NAPELLUS 10 [hp_X]/59 mL; EPINEPHRINE 10 [hp_X]/59 mL; AMMONIUM CARBONATE 10 [hp_X]/59 mL; ANTIMONY POTASSIUM TARTRATE 10 [hp_X]/59 mL; ARALIA RACEMOSA ROOT 10 [hp_X]/59 mL; BROMINE 10 mL/59 mL; CHLORINE 10 [hp_X]/59 mL; ERIODICTYON CALIFORNICUM LEAF 10 [hp_X]/59 mL; EUCALYPTUS GLOBULUS LEAF 10 [hp_X]/59 mL; GRINDELIA HIRSUTULA FLOWERING TOP 10 [hp_X]/59 mL; LOBELIA INFLATA 10 [hp_X]/59 mL; SODIUM SULFATE 10 [hp_X]/59 mL; PHOSPHORUS 10 [hp_X]/59 mL; QUEBRACHO BARK 10 [hp_X]/59 mL; TRIFOLIUM PRATENSE FLOWER 10 [hp_X]/59 mL
INACTIVE INGREDIENTS: WATER; POTASSIUM SORBATE; CITRIC ACID MONOHYDRATE

AsthmaCare

Active Ingredients

HPUS active ingredients

Equal volumes of each ingredient in 10X, 30X and LM1 potencies.

Aconitum napellus

Adrenalinum

Ammonium carbonicum

Antimonium tartaricum

Aralia racemosa

Bromium

Chlorinum

Eriodictyon californicum

Eucalyptus globulus

Grindelia

Lobelia inflata

Natrum sulphuricum

Phosphorus

Quebracho

Trifolium pratense

Reference image asthmacare.jpg

Inactive Ingredients

Purified water, potassium sorbate and citric acid.

Reference image asthmacare.jpg

Purpose

HPUS active ingredients Purpose

Equal volumes of each ingredient in 10X, 30X and LM1 potencies.

Aconitum napellus....................................................................shortness of breath

Adrenalinum.............................................................................asthma related congestion

Ammonium carbonicum............................................................breathing difficulties

Antimonium tartaricum.............................................................shortness of breath

Aralia racemosa.......................................................................tightness in chest

Bromium.................................................................................spasmodic cough

Chlorinum................................................................................tightness in chest

Eriodictyon californicum...........................................................asthmatic wheezing

Eucalyptus globulus.................................................................mucus congestion

Grindelia.................................................................................bronchial irritation

Lobelia inflata..........................................................................cough, chest discomfort

Natrum sulphuricum................................................................shortness of breath

Phosphorus............................................................................asthmatic chest spasms

Quebracho.............................................................................shortness of breath

Trifolium pratense...................................................................tracheal irritation

Reference image asthmacare.jpg

Dosage and Administration

Directions Initially, depress pump until primed. Hold close to mouth and spray one dose directly into mouth.

Adult Dose 3 pump sprays 3 times per day.

Children 6 - 12 years 2 pump sprays 3 times per day.

Use additionally as needed, up to 6 times per day.

Reference image asthmacare.jpg

Warnings

- This product is not a rescue inhaler.
- Asthma can be life threatening. If you have ever been hospitalized for asthma, consult a physician before using this product. This product is intended to complement, not replace, standard medical treatment.
- Children with asthma should be under the ongoing supervision of a physician.
- Stop use and ask a doctor if symptoms persist or worsen.
- If pregnant or breast-feeding, ask a healthcare professional before use. Keep out of reach of children.

Other information
Tamper resistant for your protection. Use only if safety seal is intact.
Reference image asthmacare.jpg

Keep out of reach of children.

Reference image asthmacare.jpg

Indications and Usage

Uses for temporary relief of minor asthma symptoms such as:

- shortness of breath
- tightness in chest
- wheezing
- bronchial irritation
- cough
- minor breathing difficulties

as per various homeopathic Materia Medicas.

PACKAGE LABEL

King Bio Inc.

3 Westside Drive

Asheville, NC 28806

www.safe-care.com

Call 800.543.3245